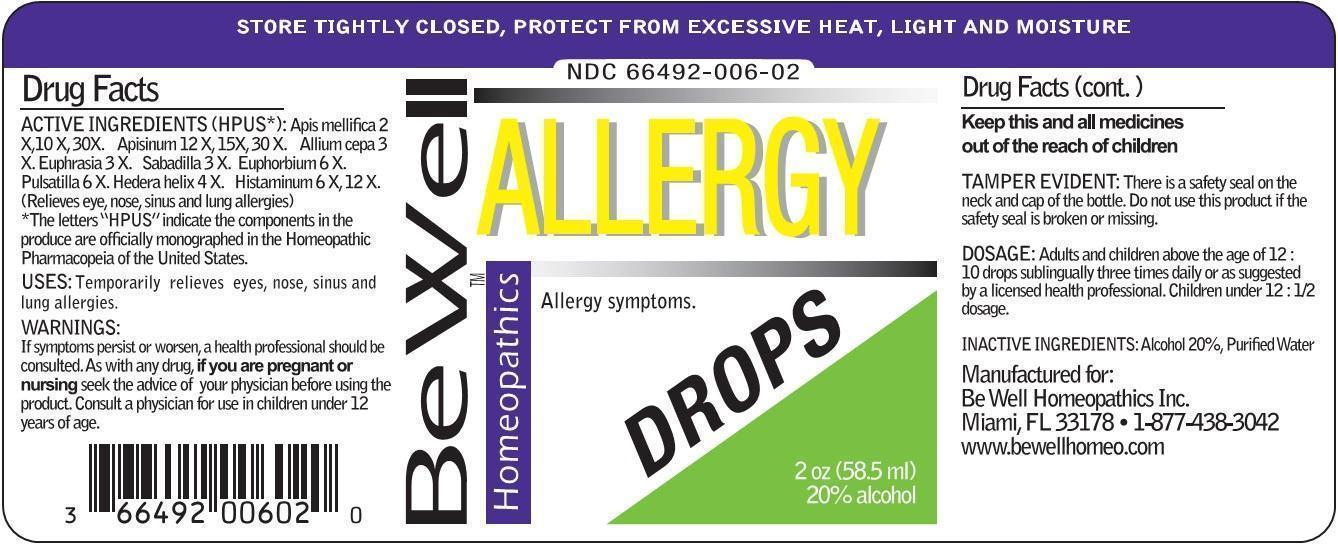 DRUG LABEL: ALLERGY DROPS
NDC: 66492-006 | Form: LIQUID
Manufacturer: Be Well Medical dba Richard Clement Nutrition y Be Well Homeopathics
Category: homeopathic | Type: HUMAN OTC DRUG LABEL
Date: 20211229

ACTIVE INGREDIENTS: APIS MELLIFERA 2 [hp_X]/1 mL; APIS MELLIFERA VENOM 12 [hp_X]/1 mL; ONION 3 [hp_X]/1 mL; EUPHRASIA STRICTA 3 [hp_X]/1 mL; SCHOENOCAULON OFFICINALE SEED 3 [hp_X]/1 mL; EUPHORBIA RESINIFERA RESIN 6 [hp_X]/1 mL; PULSATILLA VULGARIS 6 [hp_X]/1 mL; HEDERA HELIX FLOWERING TWIG 4 [hp_X]/1 mL; HISTAMINE DIHYDROCHLORIDE 6 [hp_X]/1 mL
INACTIVE INGREDIENTS: WATER; ALCOHOL

ALLERGY DROPS

ACTIVE INGREDIENT

ACTIVE INGREDIENTS (HPUS*): Apis mellifica 2X, 10X, 30X; Apisinum 12X, 15X, 30X; Allium cepa 3X; Euphrasia 3X; Sabadilla 3X; Euphorbium 6X; Pulsatilla 6X; Hedera helix 4X; Histaminum 6X, 12X. (Relieves eye, nose, sinus and lung allergies)

*The letters "HPUS" indicate the components in the produce are officially monographed in the Homeopathic Pharmacopeia of the United States.

INDICATIONS AND USAGE

USES: Temporarily relieves eyes, nose, sinus and lung allergies.

WARNINGS:

If symptoms persist or worsen, a health professional should be consulted. As with any drug, if you are pregnant or nursing seek the advice of your physician before using the product. Consult a physician for use in children under 12 years of age.

KEEP OUT OF REACH OF CHILDREN

Keep this and all medicines out of the reach of children

OTHER SAFETY INFORMATION

TAMPER EVIDENT: There is a safety seal on the neck and cap of the bottle. Do not use this product if the safety seal is broken or missing.

STORE TIGHTLY CLOSED, PROTECT FROM EXCESSIVE HEAT, LIGHT AND MOISTURE

DOSAGE AND ADMINISTRATION

DOSAGE: Adults and children above the age of 12: 10 drops sublingually three times daily or as suggested by a licensed health professional. Children under 12: 1/2 dosage.

INACTIVE INGREDIENTS: Alcohol 20%, Purified Water.

QUESTIONS

Manufactured for:

Be Well Homeopathics Inc.

Miami, FL 33178

1-877-438-3042

www.bewellhomeo.com

PACKAGE LABEL

NDC 66492-006-02

Be Well HomeopathicsTM

ALLERGY DROPS

Allergy symptoms.

2oz (58.5 ml)

20% Alcohol

PURPOSE

Allergy symptoms.